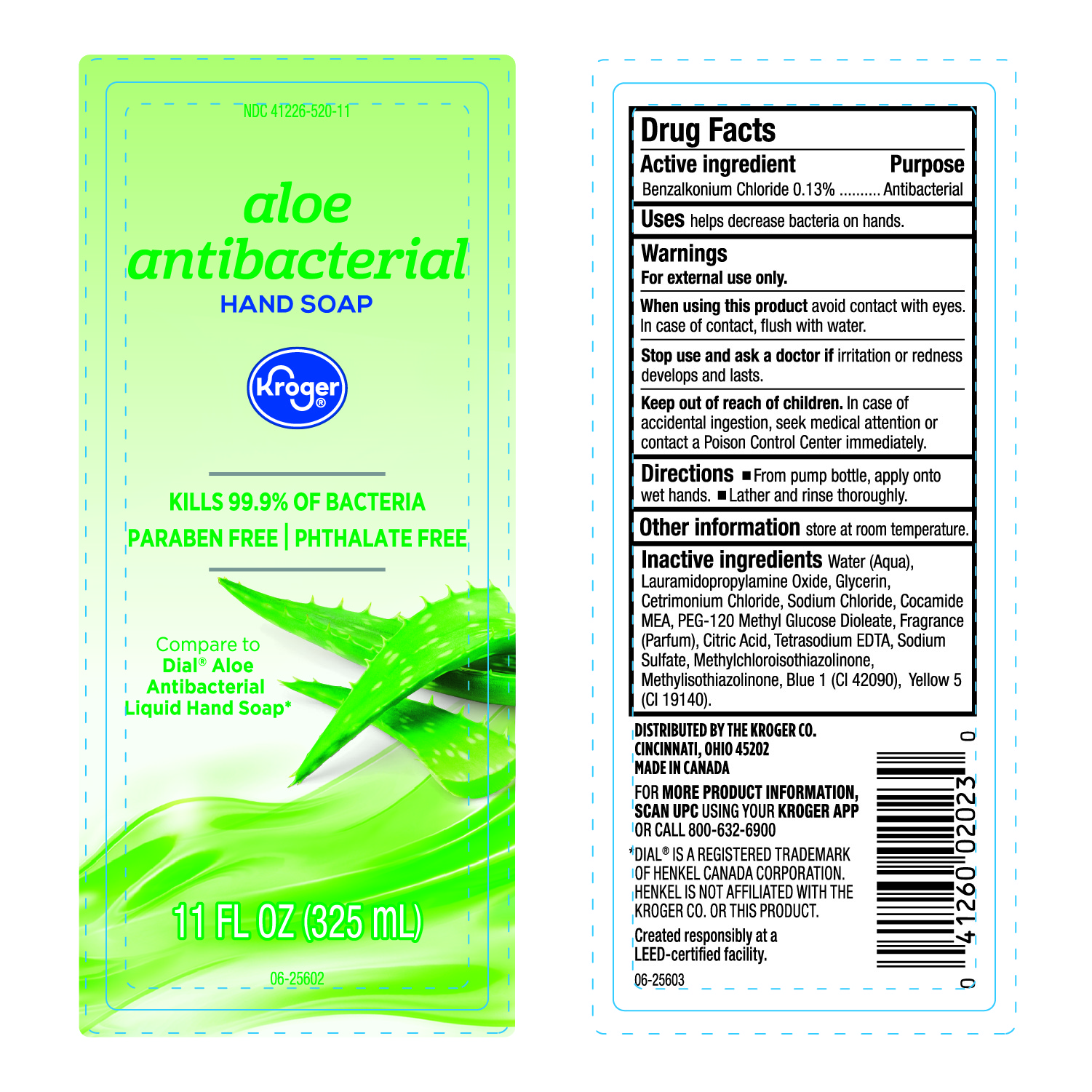 DRUG LABEL: Kroger antibacterial LHS
NDC: 41226-520 | Form: LIQUID
Manufacturer: Kroger Company
Category: otc | Type: HUMAN OTC DRUG LABEL
Date: 20250207

ACTIVE INGREDIENTS: BENZALKONIUM CHLORIDE 130 mg/100 mL
INACTIVE INGREDIENTS: CETRIMONIUM CHLORIDE; SODIUM CHLORIDE; COCO MONOETHANOLAMIDE; PEG-120 METHYL GLUCOSE DIOLEATE; EDETATE SODIUM; METHYLISOTHIAZOLINONE; FRAGRANCE CLEAN ORC0600327; FD&C BLUE NO. 1; LAURAMIDOPROPYLAMINE OXIDE; SODIUM SULFATE; GLYCERIN; CITRIC ACID MONOHYDRATE; METHYLCHLOROISOTHIAZOLINONE; FD&C YELLOW NO. 5; WATER

Kroger-Aloe Antibacterial Hand Soap

Active Ingredient

Benzalkonium Chloride 0.13%

Purpose

Antibacterial

Uses

Helps eliminate bacteria on hands.

Warnings

For external use only.

When using this product

Avoid contact with eyes. In case of Contact, Flush with Water.

Stop use and ask a doctor if

irritation or redness develops and lasts.

Keep out of reach of children.

In case of accidental ingestion, seek medical attention or contact a Poison Control Center immediately.

Directions

- From pump bottle, apply onto wet hands.
- Lather and rinse thoroughly.

Other Information

Store at Room Temperature.

Inactive Ingredients

Water (Aqua), Lauramidopropylamine Oxide, Glycerin, Cetrimonium Chloride, Sodium Chloride, Cocamide MEA, PEG-120 Methyl Glucose Dioleate, Fragrance (Parfum), Citric Acid, Tetrasodium EDTA, Sodium Sulfate, Methylchloroisothiazolinone, Methylisothiazolinone, Blue 1 (CI42090), Yellow 5 (CI 19140)